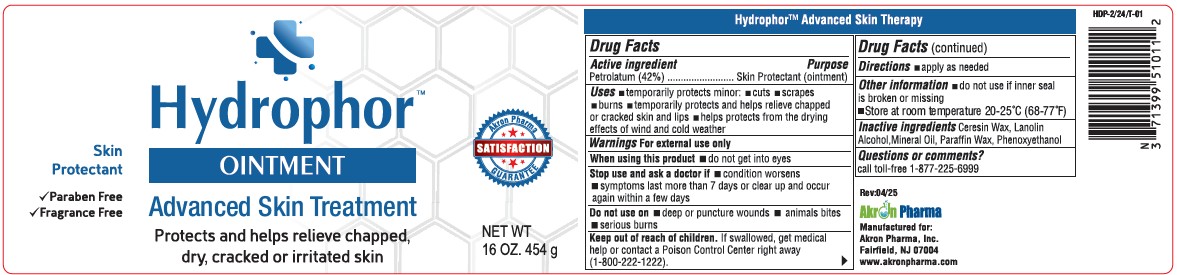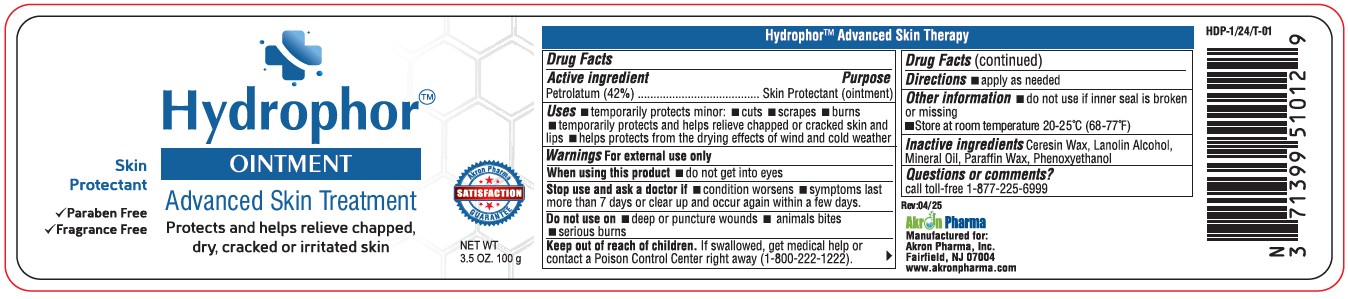 DRUG LABEL: HYDROPHOR
NDC: 71399-5101 | Form: OINTMENT
Manufacturer: Akron Pharma Inc.
Category: otc | Type: HUMAN OTC DRUG LABEL
Date: 20260119

ACTIVE INGREDIENTS: PETROLATUM 42 g/100 g
INACTIVE INGREDIENTS: CERESIN; LANOLIN; MINERAL OIL; PARAFFIN; PHENOXYETHANOL

Hydrophor Ointment

Drug Facts

Active Ingredient:

Petrolatum 42%

Purpose:

Skin protectant

Uses

temporarily protects minor:

- cuts
- scrapes
- burns

temporarily protects and helps relieve

- chapped or cracked skin and lips
- helps protects from the drying effects of wind and cold weather

Warnings

For External Use Only.

When using this product:

- do not get into eyes

Stop use and ask a doctor if

- condition worsens
- symptoms last more than 7 days or clear up and occur again within a few days

Do not use on

- deep or puncture wounds
- animals bites
- serious burns

- KEEP OUT OF REACH OF CHILDREN.

Directions

- Apply as needed.

Inactive Ingredient

Ceresin Wax, Lanolin, Mineral Oil, Paraffin Wax & Phenoxyethanol.

Other Information

- do not use if inner seal is broken or missing

Learn more at www.HydrophorUS.com

Questions?

Please Call 1(877) 225-6999

Manufactured for:

Akron Pharma, Inc.
Fairfield, NJ 07004

Manufactured in U.S.A